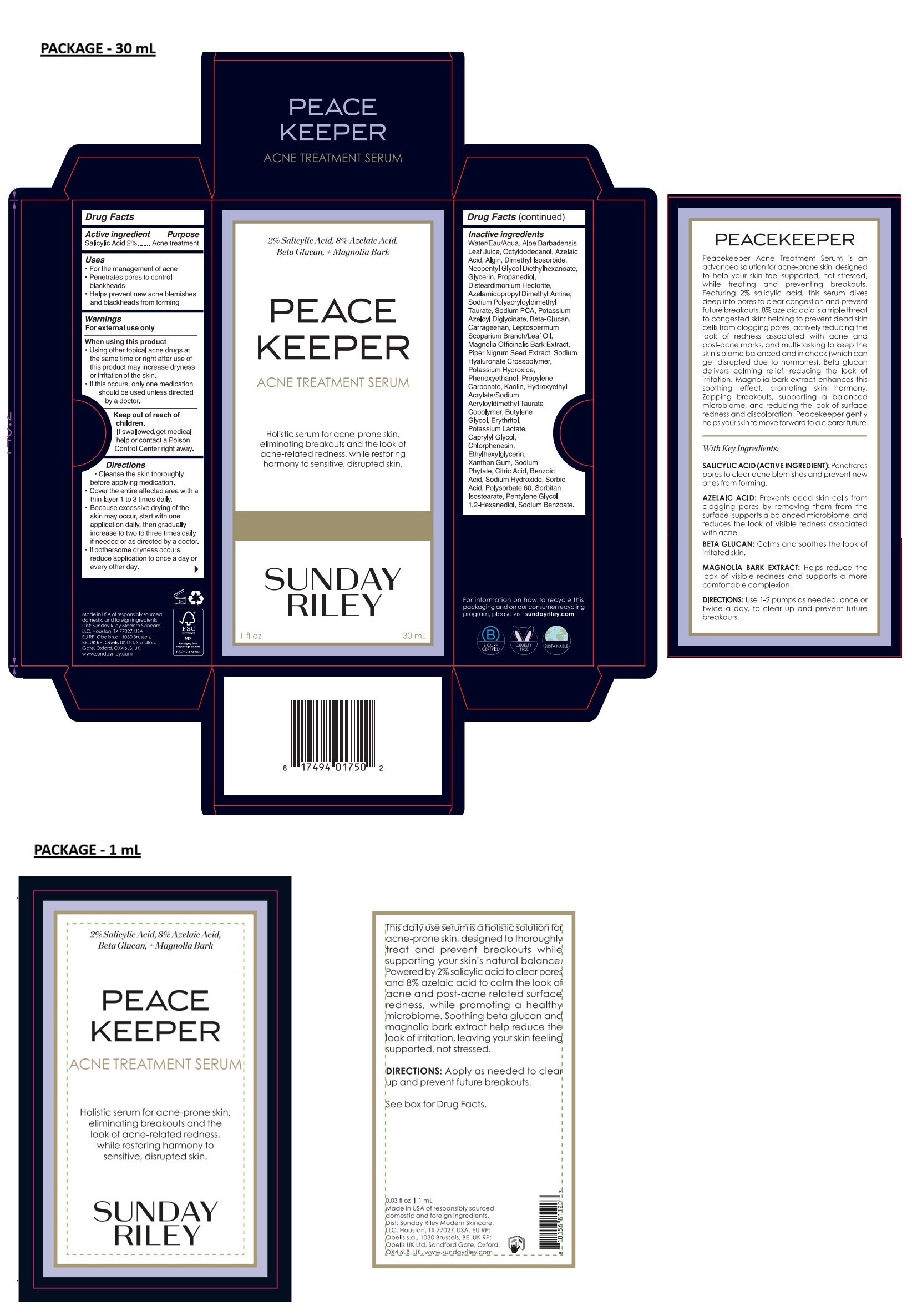 DRUG LABEL: SUNDAY RILEY PEACEKEEPER ACNE TREATMENT SERUM
NDC: 73001-505 | Form: LIQUID
Manufacturer: Sunday Riley Modern Skincare, LLC
Category: otc | Type: HUMAN OTC DRUG LABEL
Date: 20250227

ACTIVE INGREDIENTS: SALICYLIC ACID 20 mg/1 mL
INACTIVE INGREDIENTS: WATER; ALOE VERA LEAF; OCTYLDODECANOL; AZELAIC ACID; SODIUM ALGINATE; DIMETHYL ISOSORBIDE; NEOPENTYL GLYCOL DIETHYLHEXANOATE; GLYCERIN; PROPANEDIOL; DISTEARDIMONIUM HECTORITE; SODIUM POLYACRYLOYLDIMETHYL TAURATE; SODIUM PYRROLIDONE CARBOXYLATE; POTASSIUM AZELOYL DIGLYCINATE; YEAST .BETA.-D-GLUCAN; CARRAGEENAN; MANUKA OIL; MAGNOLIA OFFICINALIS BARK; BLACK PEPPER; HYALURONATE SODIUM; POTASSIUM HYDROXIDE; PHENOXYETHANOL; PROPYLENE CARBONATE; KAOLIN; HYDROXYETHYL ACRYLATE/SODIUM ACRYLOYLDIMETHYL TAURATE COPOLYMER (100000 MPA.S AT 1.5%); BUTYLENE GLYCOL; ERYTHRITOL; POTASSIUM LACTATE; CAPRYLYL GLYCOL; CHLORPHENESIN; ETHYLHEXYLGLYCERIN; XANTHAN GUM; PHYTATE SODIUM; CITRIC ACID MONOHYDRATE; BENZOIC ACID; SODIUM HYDROXIDE; SORBIC ACID; POLYSORBATE 60; SORBITAN ISOSTEARATE; PENTYLENE GLYCOL; 1,2-HEXANEDIOL; SODIUM BENZOATE

SUNDAY RILEY PEACEKEEPER ACNE TREATMENT SERUM

Active ingredient

Salicylic Acid 2%

Purpose

Acne treatment

Uses

• For the management of acne
• Penetrates pores to control blackheads
• Helps prevent new acne blemishes and blackheads from forming

Warnings

For external use only

When using this product
• Using other topical acne drugs at the same time or right after use of this product may increase dryness or irritation of the skin.
• If this occurs, only one medication should be used unless directed by a doctor.

Keep out of reach of children.
If swallowed, get medical help or contact a Poison Control Center right away.

Directions

• Cleanse the skin thoroughly before applying medication.
• Cover the entire affected area with a thin layer 1 to 3 times daily.
• Because excessive drying of the skin may occur, start with one application daily, then gradually increase to two to three times daily if needed or as directed by a doctor.
• If bothersome dryness occurs, reduce application to once a day or every other day.

Inactive ingredients

Water/Eau/Aqua, Aloe Barbadensis Leaf Juice, Octyldodecanol, Azelaic Acid, Algin, Dimethyl Isosorbide, Neopentyl Glycol Diethylhexanoate, Glycerin, Propanediol, Disteardimonium Hectorite, Azelamidopropyl Dimethyl Amine, Sodium Polyacryloyldimethyl Taurate, Sodium PCA, Potassium Azeloyl Diglycinate, Beta-Glucan, Carrageenan, Leptospermum Scoparium Branch/Leaf Oil, Magnolia Officinalis Bark Extract, Piper Nigrum Seed Extract, Sodium Hyaluronate Crosspolymer, Potassium Hydroxide, Phenoxyethanol, Propylene Carbonate, Kaolin, Hydroxyethyl Acrylate/Sodium Acryloyldimethyl Taurate Copolymer, Butylene Glycol, Erythritol, Potassium Lactate, Caprylyl Glycol, Chlorphenesin, Ethylhexylglycerin, Xanthan Gum, Sodium Phytate, Citric Acid, Benzoic Acid, Sodium Hydroxide, Sorbic Acid, Polysorbate 60, Sorbitan Isostearate, Pentylene Glycol, 1,2-Hexanediol, Sodium Benzoate.

2% Salicylic Acid, 8% Azelaic Acid,
Beta Glucan, + Magnolia Bark

Holistic serum for acne-prone skin, eliminating breakouts and the look of acne-related redness, while restoring harmony to sensitive, disrupted skin.

For information on how to recycle this packaging and on our consumer recycling program, please visit sundayriley.com

B CORP CERTIFIED

CRUELTY FREE

SUSTAINABLE

Made in USA of responsibly sourced domestic and foreign ingredients.
Dist: Sunday Riley Modern Skincare,
LLC, Houston, TX 77027, USA.
EU RP: Obelis s.a., 1030 Brussels,
BE. UK RP: Obelis UK Ltd. Sandford
Gate, Oxford, OX4 6LB, UK.
www.sundayriley.com

Peacekeeper Acne Treatment Serum is an advanced solution for acne-prone skin, designed to help your skin feel supported, not stressed, while treating and preventing breakouts. Featuring 2% salicylic acid, this serum dives deep into pores to clear congestion and prevent future breakouts. 8% azelaic acid is a triple threat to congested skin: helping to prevent dead skin cells from clogging pores, actively reducing the look of redness associated with acne and post-acne marks, and multi-tasking to keep the skin’s biome balanced and in check (which can get disrupted due to hormones). Beta glucan delivers calming relief, reducing the look of irritation. Magnolia bark extract enhances this soothing effect, promoting skin harmony. Zapping breakouts, supporting a balanced microbiome, and reducing the look of surface redness and discoloration, Peacekeeper gently helps your skin to move forward to a clearer future.

With Key Ingredients:

SALICYLIC ACID (ACTIVE INGREDIENT): Penetrates pores to clear acne blemishes and prevent new ones from forming.

AZELAIC ACID: Prevents dead skin cells from clogging pores by removing them from the surface, supports a balanced microbiome, and reduces the look of visible redness associated with acne.

BETA GLUCAN: Calms and soothes the look of irritated skin.

MAGNOLIA BARK EXTRACT: Helps reduce the look of visible redness and supports a more comfortable complexion.

DIRECTIONS: Use 1-2 pumps as needed, once or twice a day, to clear up and prevent future breakouts.

This daily use serum is a holistic solution for, acne-prone skin, designed to thoroughly treat and prevent breakouts while supporting your skin's natural balance. Powered by 2% salicylic acid to clear pores and 8% azelaic acid to calm the look of acne and post-acne related surface redness, while promoting a healthy microbiome. Soothing beta glucan and magnolia bark extract help reduce the look of irritation, leaving your skin feeling supported, not stressed.

See box for Drug Facts.